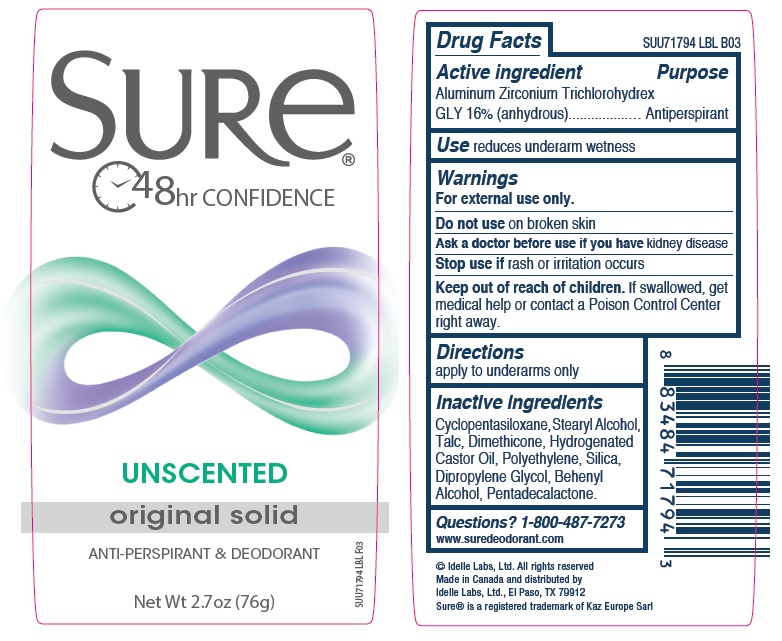 DRUG LABEL: Sure Original Solid Unscented
NDC: 41595-5513 | Form: STICK
Manufacturer: Idelle Labs, Ltd
Category: otc | Type: HUMAN OTC DRUG LABEL
Date: 20210820

ACTIVE INGREDIENTS: ALUMINUM ZIRCONIUM TRICHLOROHYDREX GLY 16 g/100 g
INACTIVE INGREDIENTS: CYCLOMETHICONE 5; STEARYL ALCOHOL; TALC; DIMETHICONE; HYDROGENATED CASTOR OIL; HIGH DENSITY POLYETHYLENE; SILICON DIOXIDE; DIPROPYLENE GLYCOL; DOCOSANOL; PENTADECALACTONE

Sure Original Solid Unscented

SURe®
48hr CONFIDENCE
UNSCENTED
original solid
ANTI-PERSPIRANT & DEODORANT
Net Wt 2.7oz (76g)

Drug Facts

Active ingredient

Aluminum Zirconium Trichlorohydrex GLY 16% (anhydrous)

Purpose

Antiperspirant

Use

Reduces underarm wetness

Warnings

For external use only.

Do not use

On broken skin

Ask a doctor before use if you have

Kidney disease

Stop use if

Rash or irritation occurs

Keep out of reach of children.

If swallowed, get medical help or contact a Poison Control Center right away.

Directions

Apply to underarms only

Inactive ingredients

Cyclopentasiloxane, Stearyl Alcohol, Talc, Dimethicone, Hydrogenated Castor Oil, Polyethylene, Silica, Dipropylene Glycol, Behenyl Alcohol, Pentadecalactone.

Questions?

1-800-487-7273
www.suredeodorant.com

© Idelle Labs, Ltd. All rights reserved
Made in Canada and distributed by
Idelle Labs, Ltd., El Paso, TX 79912
Sure® is a registered trademark of Kaz Europe Sarl